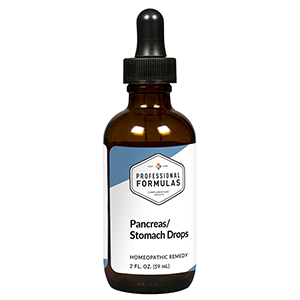 DRUG LABEL: Pancreas/Stomach Drops
NDC: 63083-5021 | Form: LIQUID
Manufacturer: Professional Complementary Health Formulas
Category: homeopathic | Type: HUMAN OTC DRUG LABEL
Date: 20190815

ACTIVE INGREDIENTS: PLANTAGO LANCEOLATA LEAF 3 [hp_X]/59 mL; GENTIANA LUTEA ROOT 5 [hp_X]/59 mL; GINGER 5 [hp_X]/59 mL; BOS TAURUS PANCREAS 6 [hp_X]/59 mL; TRIPE 6 [hp_X]/59 mL
INACTIVE INGREDIENTS: ALCOHOL; WATER

HPSD

ACTIVE INGREDIENTS

Plantago lanceolata 3X
Gentiana lutea 5X
Zingiber officinale 5X
Pancreas 6X, 12X, 30X, 60X, 100X
Stomach 6X, 12X, 30X, 60X, 100X

QUESTIONS

Professional Formulas

PO Box 2034 Lake Oswego, OR 97035

INDICATIONS

For the temporary relief of mild abdominal pain, indigestion or heartburn, bloating, nausea or vomiting, diarrhea, loss of appetite, or feelings of discomfort or uneasiness.*

PURPOSE

*Claims based on traditional homeopathic practice, not accepted medical evidence. Not FDA evaluated.

WARNINGS

Severe or persistent symptoms may be serious. Consult a doctor promptly. Keep out of the reach of children. In case of overdose, get medical help or contact a poison control center right away. If pregnant or breastfeeding, ask a healthcare professional before use.

Keep out of the reach of children.

PREGNANCY OR BREAST FEEDING

If pregnant or breastfeeding, ask a healthcare professional before use.

DIRECTIONS

Place drops under tongue 30 minutes before/after meals. Adults and children 12 years and over: Take 10 drops up to 3 times per day. Consult a physician for use in children under 12 years of age.

OTHER INFORMATION

Tamper resistant. If seal is broken, do not use. After opening, close container tightly and store at room temperature away from heat.

INACTIVE INGREDIENTS

20% ethanol, purified water.

LABEL

Est 1985

Professional Formulas

Complementary Health

Pancreas/Stomach Drops

Homeopathic Remedy

2 FL. OZ. (59 mL)